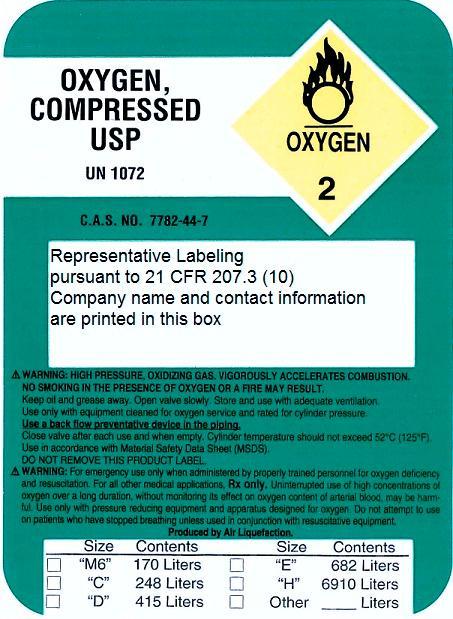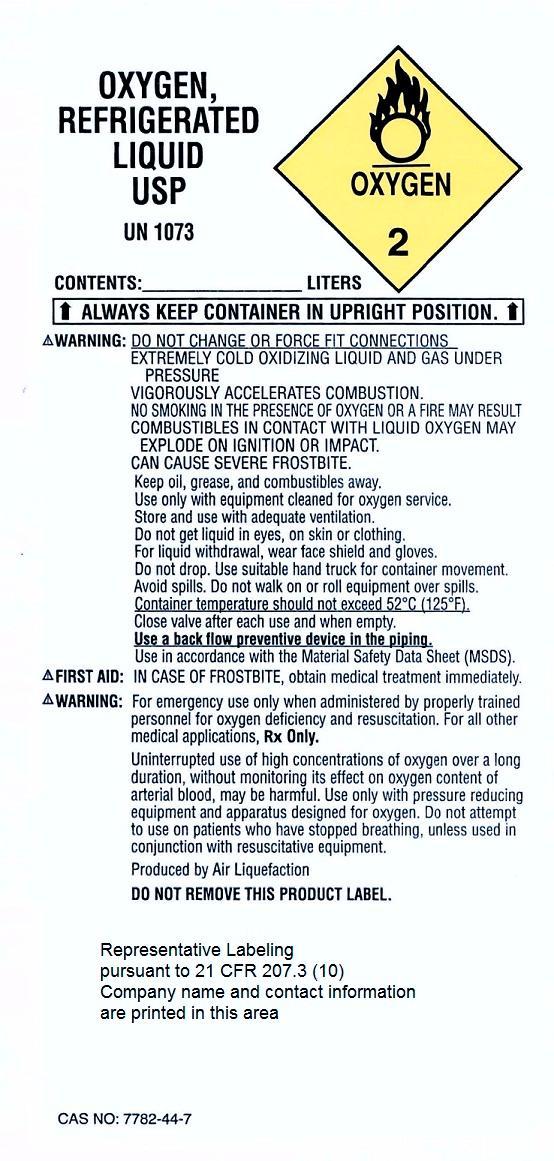 DRUG LABEL: Oxygen
NDC: 67191-001 | Form: GAS
Manufacturer: Clinical Medical Services Inc.
Category: prescription | Type: HUMAN PRESCRIPTION DRUG LABEL
Date: 20151111

ACTIVE INGREDIENTS: OXYGEN 99 L/100 L

Oxygen